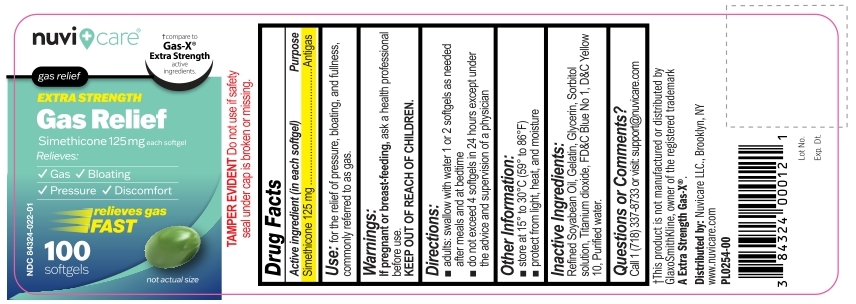 DRUG LABEL: Gas Relief
NDC: 84324-022 | Form: CAPSULE, LIQUID FILLED
Manufacturer: NUVICARE LLC
Category: otc | Type: HUMAN OTC DRUG LABEL
Date: 20250423

ACTIVE INGREDIENTS: DIMETHICONE 125 mg/1 1
INACTIVE INGREDIENTS: HYDROGENATED SOYBEAN OIL; GELATIN; GLYCERIN; SORBITOL; TITANIUM DIOXIDE; FD&C BLUE NO. 1; D&C YELLOW NO. 10; WATER

Gas Relief Simethicone 125 mg Softgels

Active ingredient (in each softgel)

Simethicone 125 mg

Purpose

Antigas

Use

For the relief of pressure, bloating, and fullness, commonly referred to as gas.

Warnings

If pregnant or breast-feeding, ask a health Professional before use .

Directions

- adults : swallow with water 1 or 2 softgels as needed after meals and at bedtime
- do not exceed 4 softgels in 24 hours except under the advice and supervision of a physician

Other Information

- store at 15 to 30ºC (59 to 86ºF)
- protect from light, heat, and moisture

Inactive Ingredients

Refined Soyabean Oil, Gelatin, Glycerin, Sorbitol solution, Titanium dioxide, FD&C lue No 1, D&C Yellow 10, Purified water.

Questions or Comments?

Call + 1 (718) 337-8733 or visit: support@nuvicare.com